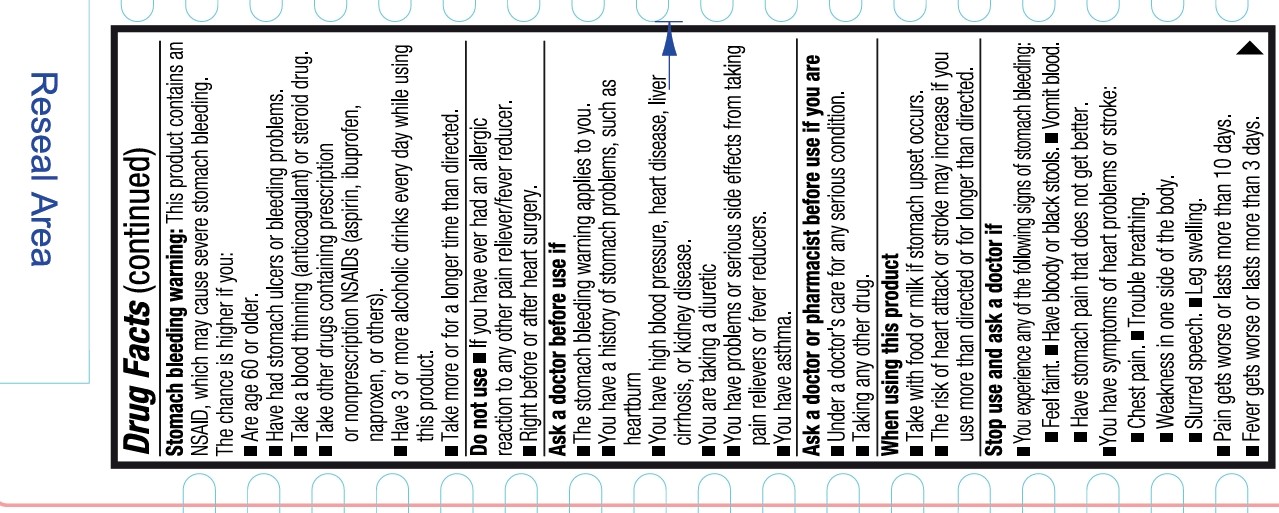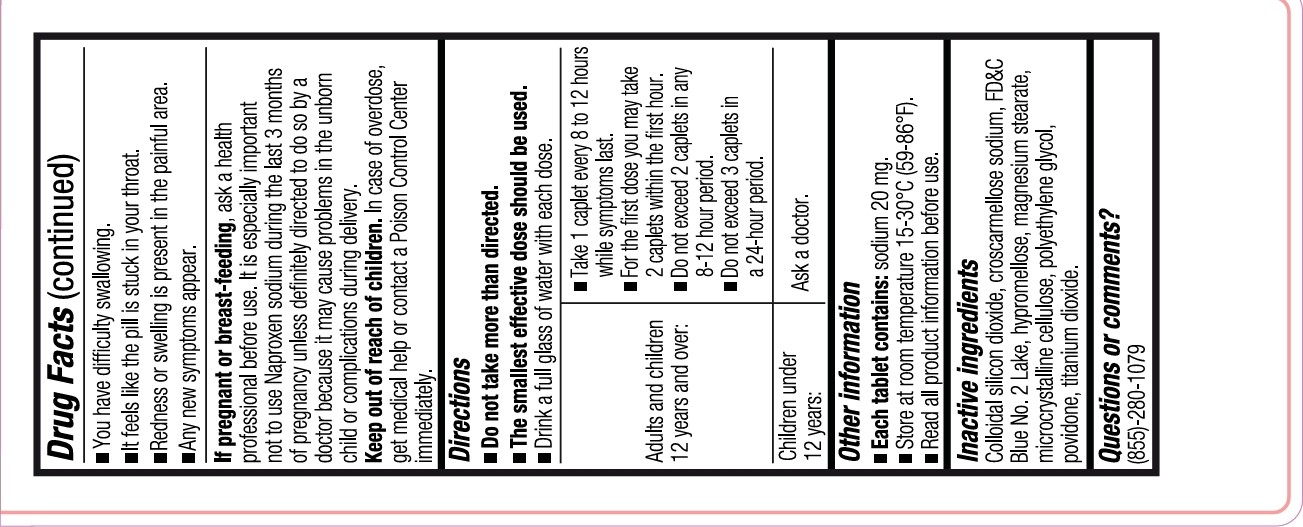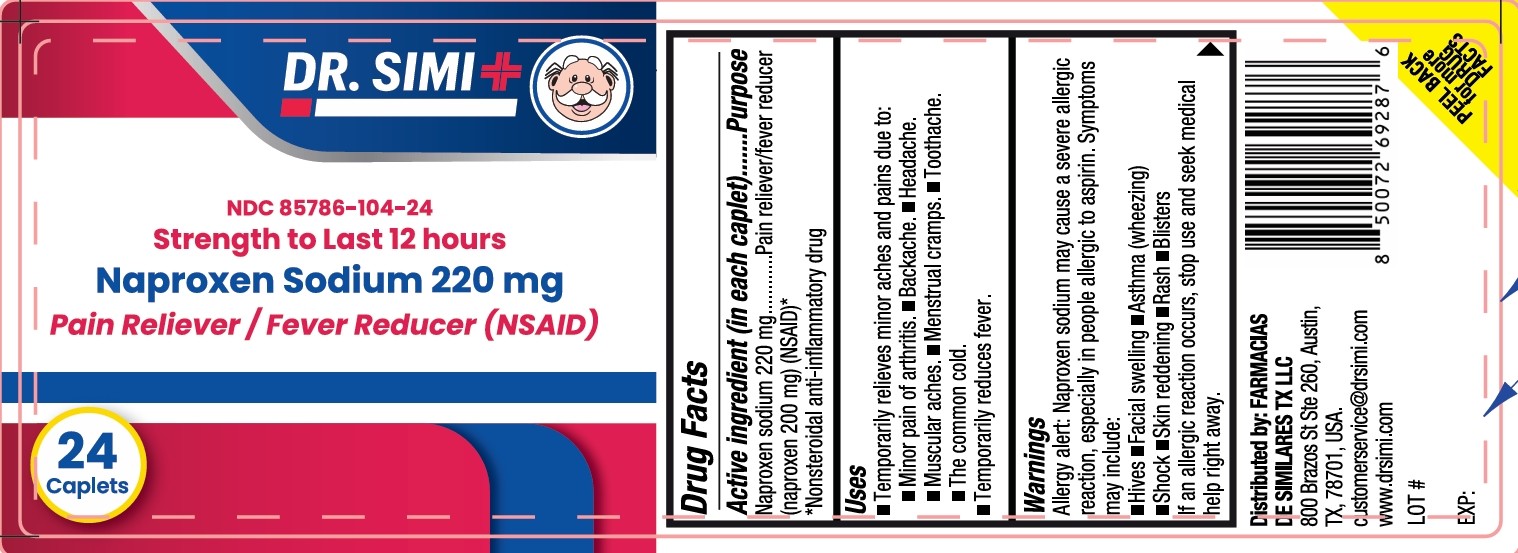 DRUG LABEL: Dr Simi All Day Pain Relief
NDC: 85786-104 | Form: TABLET, FILM COATED
Manufacturer: Farmacias De Similares TX LLC
Category: otc | Type: HUMAN OTC DRUG LABEL
Date: 20250815

ACTIVE INGREDIENTS: NAPROXEN SODIUM 220 mg/1 1
INACTIVE INGREDIENTS: HYPROMELLOSE, UNSPECIFIED; TITANIUM DIOXIDE; SILICON DIOXIDE; MAGNESIUM STEARATE; POVIDONE K30; CROSCARMELLOSE SODIUM; MICROCRYSTALLINE CELLULOSE; FD&C BLUE NO. 2 ALUMINUM LAKE; POLYETHYLENE GLYCOL, UNSPECIFIED

All day Pain Relief NAPROXEN

Drug Facts

Active ingredient (in each caplet)

- Naproxen sodium 220 mg (naproxen 200 mg) (NSAID)*

*Nonsteroidal anti-inflammatory drug

Purpose

- Pain reliever/fever reducer

Uses

- Temporarily relieves minor aches and pains due to:
- Minor pain of arthritis.
- Backache.
- Headache.
- Muscular aches.
- Menstrual cramps.
- Toothache.
- The common cold.
- Temporarily reduces fever.

Warnings

Allergy alert: Naproxen sodium may cause a severe allergic reaction, especially in people allergic to aspirin. Symptoms may include:

- Hives
- Facial swelling
- Asthma (wheezing)
- Shock
- Skin reddening
- Rash
- Blisters

If an allergic reaction occurs, stop use and seek medical help right away.

Stomach bleeding warning: This product contains an NSAID, which may cause severe stomach bleeding. The chance is higher if you:

- Are age 60 or older.
- Have had stomach ulcers or bleeding problems.
- Take a blood thinning (anticoagulant) or steroid drug.
- Take other drugs containing prescription or nonprescription NSAIDs [aspirin, ibuprofen, naproxen, or others].
- Have 3 or more alcoholic drinks every day while using this product.
- Take more or for a longer time than directed.

Do not use

- If you have ever had an allergic reaction to any other pain reliever/fever reducer.
- Right before or after heart surgery.

Ask a doctor before use if

- The stomach bleeding warning applies to you.
- You have a history of stomach problems, such as heartburn
- You have high blood pressure, heart disease, liver cirrhosis, or kidney disease.
- You are taking a diuretic
- You have problems or serious side effects from taking pain relievers or fever reducers.
- You have asthma.

Ask a doctor or pharmacist before use if you are

- Under a doctor's care for any serious condition.
- Taking any other drug.

When using this product

- Take with food or milk if stomach upset occurs.
- The risk of heart attack or stroke may increase if you use more than directed or for longer than directed.

Stop use and ask doctor if

- You experience any of the following signs of stomach bleeding:
  - Feel faint.
  - Have bloody or black stools.
  - Vomit blood.
  - Have stomach pain that does not get better.
- You have symptoms of heart problems or stroke:
- Chest Pain
- Trouble breathing
- Weakness in one side of the body
- Slurred speech
- Leg swelling
- Pain gets worse or lasts more than 10 days.
- Fever gets worse or lasts more than 3 days.
- You have difficulty swallowing.
- It feels like the pill is stuck in your throat.
- Redness or swelling is present in the painful area.
- Any new symptoms appear.

If pregnant or breast-feeding

ask a health professional before use. It is especially important not to use Naproxen sodium during the last 3 months of pregnancy unless definitely directed to do so by a doctor because it may cause problems in the unborn child or complications during delivery.

Keep out of reach of children

OVERDOSAGE

In case of overdose, get medical help or contact a Poison Control Center immediately.

Directions

- Do not take more than directed.
- The smallest effective dose should be used
- Drink a full glass of water with each dose.

DOSAGE AND ADMINISTRATION

Adults and children 12 years and over: | - Take 1 caplet every 8 to 12 hours while symptoms last. - For the first dose you may take 2 caplets within the first hour. - Do not exceed 2 caplets in any 8-12 hour period. - Do not exceed 3 caplets in a 24-hour period.
Children under 12 years: | Ask a doctor.

Other information

- Each tablet contains: sodium 20 mg.
- Store at room temperature 15-30°C (59-86°F).
- Read all product information before use.

Inactive ingredients

Colloidal silicon dioxide, croscarmellose sodium, FD&C Blue No. 2 Lake, hypromellose, magnesium stearate, mirocrystalline cellulose, polyethylene glycol, povidone, titanium dioxide.

Questions or comments?

(855)-280-1079

Distributed by: FARMACIAS DE SIMILARES TX LLC
800 Brazos St Ste 260, Austin, TX, 78701, USA.
customerservice@drsimi.com
www.drsimi.com

LOT #

EXP:

PEEL BACK for more DRUG FACTS

PACKAGE LABEL

DR SIMI

NDC 85786-104-24

Strength to Last 12 hours

Naproxen Sodium 220 mg

Pain Reliever/Fever Reducer (NSAID)

24 Caplets